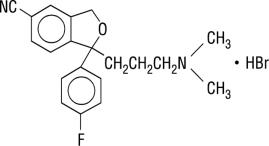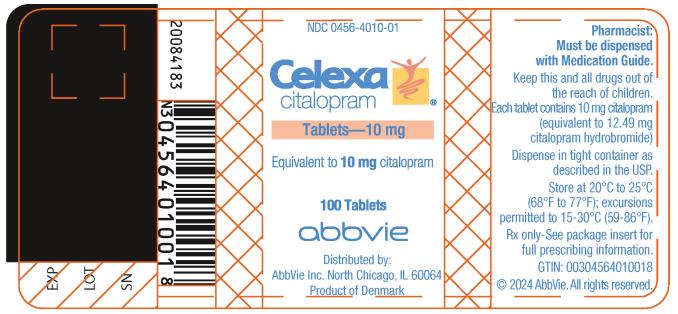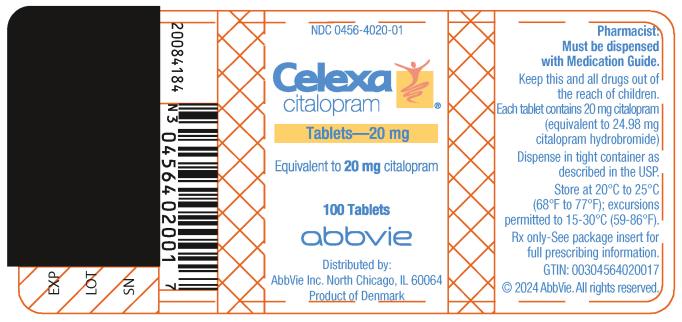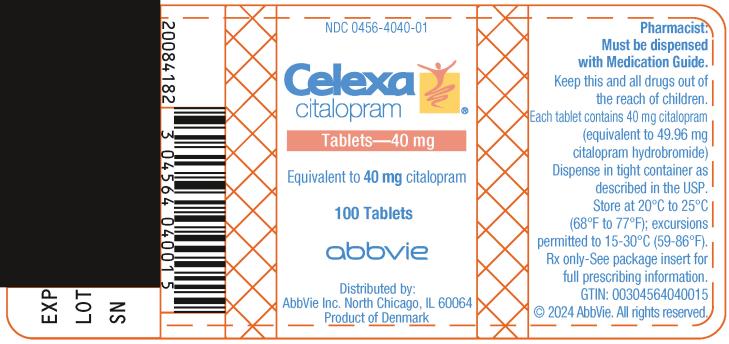 DRUG LABEL: Celexa
NDC: 0456-4010 | Form: TABLET, FILM COATED
Manufacturer: Allergan, Inc.
Category: prescription | Type: HUMAN PRESCRIPTION DRUG LABEL
Date: 20231009

ACTIVE INGREDIENTS: CITALOPRAM HYDROBROMIDE 10 mg/1 1
INACTIVE INGREDIENTS: COPOVIDONE K25-31; starch, corn; croscarmellose sodium; glycerin; lactose monohydrate; magnesium stearate; hypromelloses; cellulose, microcrystalline; POLYETHYLENE GLYCOL, UNSPECIFIED; titanium dioxide; FERRIC OXIDE RED; FERRIC OXIDE YELLOW

HIGHLIGHTS OF PRESCRIBING INFORMATION

These highlights do not include all the information needed to use CELEXA® safely and effectively. See full prescribing information for CELEXA®.
CELEXA (citalopram) tablets, for oral use
Initial U.S. Approval: 1998

RECENT MAJOR CHANGES

Warnings and Precautions (5.3, 5.4) 08/2023

WARNING: SUICIDAL THOUGHTS AND BEHAVIORS

See full prescribing information for complete boxed warning.

- Increased risk of suicidal thoughts and behavior in pediatric and young adult patients taking antidepressants. Closely monitor all antidepressant-treated patients for clinical worsening and emergence of suicidal thoughts and behaviors (5.1).
- CELEXA is not approved for use in pediatric patients (8.4).

1 INDICATIONS AND USAGE

CELEXA is a selective serotonin reuptake inhibitor (SSRI) indicated for the treatment of major depressive disorder (MDD) in adults (1).

2 DOSAGE AND ADMINISTRATION

- Administer once daily with or without food (2).
- Initial dosage is 20 mg once daily; after one week may increase to maximum dosage of 40 mg once daily (2.1).
- Patients greater than 60 years of age, patients with hepatic impairment, and CYP2C19 poor metabolizers: maximum recommended dosage is 20 mg once daily (2.2).
- When discontinuing CELEXA, reduce dosage gradually (2.4, 5.6).

3 DOSAGE FORMS AND STRENGTHS

Tablets: 10 mg; 20 mg, scored; and 40 mg, scored (3)

4 CONTRAINDICATIONS

- Concomitant use of monoamine oxidase inhibitors (MAOIs) or use within 14 days of discontinuing a MAOI (4).
- Concomitant use of pimozide (4).
- Known hypersensitivity to citalopram or any of the inactive ingredients of CELEXA (4).

5 WARNINGS AND PRECAUTIONS

- QT-Prolongation and Torsade de Pointes: Dose-dependent QTc prolongation, Torsade de pointes, ventricular tachycardia, and sudden death have occurred. Avoid use of CELEXA in patients with congenital long QT syndrome, bradycardia, hypokalemia or hypomagnesemia, recent acute myocardial infarction, or uncompensated heart failure and patients taking other drugs that prolong the QTc interval. Monitor electrolytes in patients at high risk for hypokalemia or hypomagnesemia. Discontinue CELEXA in patients with persistent QTc measurements > 500 ms (5.2, 7).
- Serotonin Syndrome: Increased risk when co-administered with other serotonergic agents, but also when taken alone. If occurs, discontinue CELEXA and serotonergic agents and initiate supportive measures (5.3).
- Increased Risk of Bleeding: Concomitant use of aspirin, nonsteroidal anti-inflammatory drugs, other antiplatelet drugs, warfarin and other anticoagulants may increase this risk (5.4).
- Activation of Mania/Hypomania: Screen patients for bipolar disorder (5.5).
- Seizures: Use with caution in patients with seizure disorder (5.7).
- Angle-Closure Glaucoma: Avoid use of CELEXA in patients with untreated anatomically narrow angles (5.8).
- Hyponatremia: Can occur in association with syndrome of inappropriate antidiuretic hormone secretion (5.9).
- Sexual Dysfunction: CELEXA may cause symptoms of sexual dysfunction (5.10).

6 ADVERSE REACTIONS

Most common adverse reaction (incidence ≥ 5% and twice placebo) is ejaculation disorder (primarily ejaculation delay) (6.1).

To report SUSPECTED ADVERSE REACTIONS, contact AbbVie at 1-800-678-1605 or FDA at 1-800-FDA-1088 or www.fda.gov/medwatch.

7 DRUG INTERACTIONS

CYP2C19 Inhibitors: CELEXA 20 mg daily is the maximum recommended dosage for patients taking concomitant CYP2C19 inhibitors (5.2, 7.1).

8 USE IN SPECIFIC POPULATIONS

- Pregnancy: SSRI use, particularly late in pregnancy, may increase the risk for persistent pulmonary hypertension and symptoms of poor adaptation (respiratory distress, temperature instability, feeding difficulties, hypotonia, tremor, irritability) in the neonate (8.1).

FULL PRESCRIBING INFORMATION

WARNING: SUICIDAL THOUGHTS AND BEHAVIORS

Antidepressants increased the risk of suicidal thoughts and behaviors in pediatric and young adult patients in short-term studies. Closely monitor all antidepressant-treated patients for clinical worsening, and for emergence of suicidal thoughts and behaviors [see Warnings and Precautions (5.1)]. CELEXA is not approved for use in pediatric patients [see Use in Specific Populations (8.4)].

1 INDICATIONS AND USAGE

CELEXA is indicated for the treatment of major depressive disorder (MDD) in adults [see Clinical Studies (14)].

2 DOSAGE AND ADMINISTRATION

2.1 Recommended Dosage

Administer CELEXA once daily, with or without food, at an initial dosage of 20 mg once daily, with an increase to a maximum dosage of 40 mg once daily at an interval of no less than one week.

Dosages above 40 mg once daily are not recommended due to the risk of QT prolongation [see Warnings and Precautions (5.2)].

2.2 Screen for Bipolar Disorder Prior to Starting CELEXA

Prior to initiating treatment with CELEXA or another antidepressant, screen patients for a personal or family history of bipolar disorder, mania, or hypomania [See Warnings and Precautions (5.5)].

2.3 Recommended Dosage for Specific Populations

The maximum recommended dosage of CELEXA for patients who are greater than 60 years of age, patients with hepatic impairment, and for CYP2C19 poor metabolizers is 20 mg once daily [see Warnings and Precautions (5.2), Clinical Pharmacology (12.3)].

2.4 Dosage Modifications with Concomitant Use of CYP2C19 Inhibitors

The maximum recommended dosage of CELEXA when used concomitantly with a CYP2C19 inhibitor is 20 mg once daily [see Warnings and Precautions (5.2), Drug Interactions (7)].

2.5 Switching Patients to or from a Monoamine Oxidase Inhibitor Antidepressant

At least 14 days must elapse between discontinuation of a monoamine oxidase inhibitor (MAOI) antidepressant and initiation of therapy with CELEXA. Conversely, at least 14 days must elapse after stopping CELEXA before starting an MAOI antidepressant [see Contraindications (4) and Warnings and Precautions (5.3)].

2.6 Discontinuing Treatment with CELEXA

Adverse reactions may occur upon discontinuation of CELEXA [see Warnings and Precautions (5.6)]. Gradually reduce the dosage rather than stopping CELEXA abruptly whenever possible.

3 DOSAGE FORMS AND STRENGTHS

CELEXA tablets are available as:

- 10 mg: beige, oval with “FP” imprinted on one side, “10 mg” imprinted on the other side
- 20 mg: pink, oval, scored with “F” imprinted on left side of score line and "P" imprinted on right side of score line, “20 mg” imprinted on non-scored side
- 40 mg: white, oval, scored with “F” imprinted on left side of score line and "P" imprinted on right side of score line, “40 mg” imprinted on non-scored side

4 CONTRAINDICATIONS

CELEXA is contraindicated in patients:

- taking, or within 14 days of stopping, MAOIs (including MAOIs such as linezolid or intravenous methylene blue) because of an increased risk of serotonin syndrome [see Warnings and Precautions (5.3), Drug Interactions (7)].
- taking pimozide because of risk of QT prolongation [see Drug Interactions (7)].
- with known hypersensitivity to citalopram or any of the inactive ingredients in CELEXA. Reactions have included angioedema and anaphylaxis [see Adverse Reactions (6.2)].

5 WARNINGS AND PRECAUTIONS

5.1 Suicidal Thoughts and Behavior in Adolescents and Young Adults

In pooled analyses of placebo-controlled trials of antidepressant drugs (SSRIs and other antidepressant classes) that included approximately 77,000 adult patients, and 4,500 pediatric patients, the incidence of suicidal thoughts and behaviors in antidepressant-treated patients age 24 years and younger was greater than in placebo-treated patients. There was considerable variation in risk of suicidal thoughts and behaviors among drugs, but there was an increased risk identified in young patients for most drugs studied. There were differences in absolute risk of suicidal thoughts and behaviors across the different indications, with the highest incidence in patients with MDD. The drug-placebo differences in the number of cases of suicidal thoughts and behaviors per 1000 patients treated are provided in Table 1.

Table 1: Risk Differences of the Number of Patients with Suicidal Thoughts and Behaviors in the Pooled Placebo-Controlled Trials of Antidepressants in Pediatric and Adult Patients
Age Range* | Drug-Placebo Difference in Number of Patients with Suicidal Thoughts or Behaviors per 1000 Patients Treated
 | Increases Compared to Placebo
<18 years old | 14 additional patients
18-24 years old | 5 additional patients
 | Decreases Compared to Placebo
25-64 years old | 1 fewer patient
≥65 years old | 6 fewer patients

*CELEXA is not approved for use in pediatric patients.

It is unknown whether the risk of suicidal thoughts and behaviors in children, adolescents, and young adults extends to longer-term use, i.e., beyond four months. However, there is substantial evidence from placebo-controlled maintenance trials in adults with MDD that antidepressants delay the recurrence of depression and that depression itself is a risk factor for suicidal thoughts and behaviors.

Monitor all antidepressant-treated patients for clinical worsening and emergence of suicidal thoughts and behaviors, especially during the initial few months of drug therapy and at times of dosage changes. Counsel family members or caregivers of patients to monitor for changes in behavior and to alert the healthcare provider. Consider changing the therapeutic regimen, including possibly discontinuing CELEXA, in patients whose depression is persistently worse, or who are experiencing emergent suicidal thoughts or behaviors.

5.2 QT-Prolongation and Torsade de Pointes

CELEXA causes dose-dependent QTc prolongation an ECG abnormality that has been associated with Torsade de Pointes (TdP), ventricular tachycardia, and sudden death, all of which have been observed in postmarketing reports for citalopram [see Adverse Reactions (6.2)].

Because of the risk of QTc prolongation at higher CELEXA doses, it is recommended that CELEXA not be given at doses above 40 mg once daily [see Dosage and Administration (2.1), Clinical Pharmacology (12.2)].

CELEXA should be avoided in patients with congenital long QT syndrome, bradycardia, hypokalemia or hypomagnesemia, recent acute myocardial infarction, or uncompensated heart failure unless the benefits outweigh the risks for a particular patient. CELEXA should also be avoided in patients who are taking other drugs that prolong the QTc interval [see Drug Interactions (7)]. Such drugs include Class 1A (e.g., quinidine, procainamide) or Class III (e.g., amiodarone, sotalol) antiarrhythmic medications, antipsychotic medications (e.g., chlorpromazine, thioridazine), antibiotics (e.g., gatifloxacin, moxifloxacin), or any other class of medications known to prolong the QTc interval (e.g., pentamidine, levomethadyl acetate, methadone).

The citalopram dose should be limited in certain populations. The maximum dose should be limited to 20 mg once daily in patients who are CYP2C19 poor metabolizers or those patients receiving concomitant cimetidine or another CYP2C19 inhibitor, since higher citalopram exposures would be expected. The maximum dose should also be limited to 20 mg once daily in patients with hepatic impairment and in patients who are greater than 60 years of age because of expected higher exposures [see Dosage and Administration (2.3, 2.4), Drug Interactions (7), Use in Specific Populations (8.5), Clinical Pharmacology (12.3)].

Electrolyte and/or ECG monitoring is recommended in certain circumstances. Patients being considered for treatment with CELEXA who are at risk for significant electrolyte disturbances should have baseline serum potassium and magnesium measurements with periodic monitoring. Hypokalemia (and/or hypomagnesemia) may increase the risk of QTc prolongation and arrhythmia, and should be corrected prior to initiation of treatment and periodically monitored. ECG monitoring is recommended in patients for whom CELEXA use is not recommended unless the benefits clearly outweigh the risks for a particular patient (see above). These include those patients with the cardiac conditions noted above, and those taking other drugs that may prolong the QTc interval.

Discontinue CELEXA in patients who are found to have persistent QTc measurements >500 ms. If patients taking CELEXA experience symptoms that could indicate the occurrence of cardiac arrhythmias, e.g., dizziness, palpitations, or syncope, the prescriber should initiate further evaluation, including cardiac monitoring.

5.3 Serotonin Syndrome

SSRIs, including CELEXA, can precipitate serotonin syndrome, a potentially life-threatening condition. The risk is increased with concomitant use of other serotonergic drugs (including triptans, tricyclic antidepressants, fentanyl, lithium, tramadol, meperidine, methadone, tryptophan, buspirone, amphetamines, and St. John’s Wort) and with drugs that impair metabolism of serotonin, i.e., MAOIs [see Contraindications (4), Drug Interactions (7)]. Serotonin syndrome can also occur when these drugs are used alone. Symptoms of serotonin syndrome were noted in 0.1% of MDD patients treated with CELEXA in premarketing clinical trials.

Serotonin syndrome signs and symptoms may include mental status changes (e.g., agitation, hallucinations, delirium, and coma), autonomic instability (e.g., tachycardia, labile blood pressure, dizziness, diaphoresis, flushing, hyperthermia), neuromuscular symptoms (e.g., tremor, rigidity, myoclonus, hyperreflexia, incoordination), seizures, and gastrointestinal symptoms (e.g., nausea, vomiting, diarrhea).

The concomitant use of CELEXA with MAOIs is contraindicated. In addition, do not initiate CELEXA in a patient being treated with MAOIs such as linezolid or intravenous methylene blue. No reports involved the administration of methylene blue by other routes (such as oral tablets or local tissue injection). If it is necessary to initiate treatment with an MAOI such as linezolid or intravenous methylene blue in a patient taking CELEXA, discontinue CELEXA before initiating treatment with the MAOI [see Contraindications (4), Drug Interactions (7)].

Monitor all patients taking CELEXA for the emergence of serotonin syndrome. Discontinue treatment with CELEXA and any concomitant serotonergic agents immediately if the above symptoms occur, and initiate supportive symptomatic treatment. If concomitant use of CELEXA with other serotonergic drugs is clinically warranted, inform patients of the increased risk for serotonin syndrome and monitor for symptoms.

5.4 Increased Risk of Bleeding

Drugs that interfere with serotonin reuptake inhibition, including CELEXA, increase the risk of bleeding events. Concomitant use of aspirin, nonsteroidal anti-inflammatory drugs (NSAIDS), other antiplatelet drugs, warfarin, and other anticoagulants may add to this risk. Case reports and epidemiological studies (case-control and cohort design) have demonstrated an association between use of drugs that interfere with serotonin reuptake and the occurrence of gastrointestinal bleeding. Based on data from the published observational studies, exposure to SSRIs, particularly in the month before delivery, has been associated with a less than 2-fold increase in the risk of postpartum hemorrhage [see Use in Specific Populations (8.1)]. Bleeding events related to drugs that interfere with serotonin reuptake have ranged from ecchymosis, hematoma, epistaxis, and petechiae to life-threatening hemorrhages.

Inform patients about the increased risk of bleeding associated with the concomitant use of CELEXA and antiplatelet agents or anticoagulants. For patients taking warfarin, carefully monitor the international normalized ratio [see Drug Interactions (7)].

5.5 Activation of Mania or Hypomania

In patients with bipolar disorder, treating a depressive episode with CELEXA or another antidepressant may precipitate a mixed/manic episode. In controlled clinical trials, patients with bipolar disorder were excluded; however, symptoms of mania or hypomania were reported in 0.1% of undiagnosed patients treated with CELEXA. Prior to initiating treatment with CELEXA, screen patients for any personal or family history of bipolar disorder, mania, or hypomania [see Dosage and Administration (2.2)].

5.6 Discontinuation Syndrome

Adverse reactions after discontinuation of serotonergic antidepressants, particularly after abrupt discontinuation, include: nausea, sweating, dysphoric mood, irritability, agitation, dizziness, sensory disturbances (e.g., paresthesia, such as electric shock sensations), tremor, anxiety, confusion, headache, lethargy, emotional lability, insomnia, hypomania, tinnitus, and seizures. A gradual reduction in dosage rather than abrupt cessation is recommended whenever possible [see Dosage and Administration (2.6)].

5.7 Seizures

CELEXA has not been systematically evaluated in patients with seizure disorders. Patients with a history of seizures were excluded from clinical studies. In clinical trials of CELEXA, seizures occurred in 0.3% of patients treated with CELEXA (a rate of one patient per 98 years of exposure) and 0.5% of patients treated with placebo (a rate of one patient per 50 years of exposure). CELEXA should be prescribed with caution in patients with a seizure disorder.

5.8 Angle-closure Glaucoma

The pupillary dilation that occurs following use of many antidepressant drugs, including CELEXA, may trigger an angle closure attack in a patient with anatomically narrow angles who does not have a patent iridectomy. Avoid use of antidepressants, including CELEXA, in patients with untreated anatomically narrow angles.

5.9 Hyponatremia

Hyponatremia may occur as a result of treatment with SSRIs, including CELEXA. Cases of serum sodium lower than 110 mmol/L have been reported. Signs and symptoms of hyponatremia include headache, difficulty concentrating, memory impairment, confusion, weakness, and unsteadiness, which may lead to falls. Signs and symptoms associated with more severe and/or acute cases have included hallucination, syncope, seizure, coma, respiratory arrest, and death. In many cases, this hyponatremia appears to be the result of the syndrome of inappropriate antidiuretic hormone secretion (SIADH).

In patients with symptomatic hyponatremia, discontinue CELEXA and institute appropriate medical intervention. Elderly patients, patients taking diuretics, and those who are volume-depleted may be at greater risk of developing hyponatremia with SSRIs [see Use in Specific Populations (8.5)].

5.10 Sexual Dysfunction

Use of SSRIs, including CELEXA, may cause symptoms of sexual dysfunction [see Adverse Reactions (6.1)]. In male patients, SSRI use may result in ejaculatory delay or failure, decreased libido, and erectile dysfunction. In female patients, SSRI use may result in decreased libido and delayed or absent orgasm.

It is important for prescribers to inquire about sexual function prior to initiation of CELEXA and to inquire specifically about changes in sexual function during treatment, because sexual function may not be spontaneously reported. When evaluating changes in sexual function, obtaining a detailed history (including timing of symptom onset) is important because sexual symptoms may have other causes, including the underlying psychiatric disorder. Discuss potential management strategies to support patients in making informed decisions about treatment.

6 ADVERSE REACTIONS

The following adverse reactions are discussed in greater detail in other sections of the labeling:

- Hypersensitivity reactions [see Contraindications (4)]
- Suicidal thoughts and behaviors in adolescents and young adults [see Warnings and Precautions (5.1)]
- QT-prolongation and torsade de pointes [see Warnings and Precautions (5.2)]
- Serotonin syndrome [see Warnings and Precautions (5.3)]
- Increased risk of bleeding [see Warnings and Precautions (5.4)]
- Activation of mania or hypomania [see Warnings and Precautions (5.5)]
- Discontinuation syndrome [see Warnings and Precautions (5.6)]
- Seizures [see Warnings and Precautions (5.7)]
- Angle-closure glaucoma [see Warnings and Precautions (5.8)]
- Hyponatremia [see Warnings and Precautions (5.9)]
- Sexual Dysfunction [see Warnings and Precautions (5.10)]

6.1 Clinical Trials Experience

Because clinical trials are conducted under widely varying conditions, adverse reaction rates observed in the clinical trials of a drug cannot be directly compared to rates in the clinical studies of another drug and may not reflect the rates observed in clinical practice.

The safety for CELEXA included citalopram exposures in patients and/or healthy subjects from 3 different groups of studies: 429 healthy subjects in clinical pharmacology/pharmacokinetic studies; 4,422 exposures from patients in controlled and uncontrolled clinical trials, corresponding to approximately 1,370 patient-exposure years. There were, in addition, over 19,000 exposures from mostly open-label, European postmarketing studies. The conditions and duration of treatment with CELEXA varied greatly and included (in overlapping categories) open-label and double-blind studies, inpatient and outpatient studies, fixed-dose and dose-titration studies, and short-term and long-term exposure.

Adverse Reactions Associated with Discontinuation of Treatment

Among 1,063 patients with MDD who received CELEXA at doses ranging from 10 mg to 80 mg once daily in placebo-controlled trials of up to 6 weeks duration, 16% discontinued treatment due to an adverse reaction, as compared to 8% of 446 patients receiving placebo. The adverse reactions associated with discontinuation (i.e., associated with discontinuation in at least 1% of CELEXA-treated patients at a rate at least twice that of placebo) are shown in Table 2.

Table 2: Adverse Reactions Associated with Discontinuation of CELEXA Treatment in Short-Term, Placebo-Controlled MDD Trials
Body System/Adverse Reaction | CELEXA | Placebo
 | (N=1,063) % | (N=446) %
General
Asthenia | 1 | <1
Gastrointestinal Disorders
Nausea | 4 | 0
Dry Mouth | 1 | <1
Vomiting | 1 | 0
Central and Peripheral Nervous System Disorders
Dizziness | 2 | <1
Psychiatric Disorders
Insomnia | 3 | 1
Somnolence | 2 | 1
Agitation | 1 | <1

* A patient can report more than one reason for discontinuation and be counted more than once in this table.

Table 3 enumerates the incidence of adverse reactions that occurred among 1,063 patients with MDD who received CELEXA at doses ranging from 10 mg to 80 mg once daily in placebo-controlled trials of up to 6 weeks duration.

The most common adverse reaction that occurred in CELEXA-treated patients with an incidence of 5% or greater and at least twice the incidence in placebo patients was ejaculation disorder (primarily ejaculatory delay) in male patients (see Table 3).

Table 3: Adverse Reactions (≥2% and Greater than Placebo) Among CELEXA-Treated Patients*
 | CELEXA | Placebo
Body System/Adverse Reaction | (N=1,063) % | (N=446) %
Gastrointestinal Disorders
Nausea | 21 | 14
Diarrhea | 8 | 5
Dyspepsia | 5 | 4
Vomiting | 4 | 3
Abdominal Pain | 3 | 2
Autonomic Nervous System Disorders
Dry Mouth | 20 | 14
Sweating Increased | 11 | 9
Psychiatric Disorders
Somnolence | 18 | 10
Insomnia | 15 | 14
Anxiety | 4 | 3
Anorexia | 4 | 2
Agitation | 3 | 1
Dysmenorrhea^1 | 3 | 2
Libido Decreased | 2 | <1
Yawning | 2 | <1
Central & Peripheral Nervous System Disorders
Tremor | 8 | 6
Urogenital
Ejaculation Disorder^2,3 | 6 | 1
Impotence^3 | 3 | <1
Respiratory System Disorders
Upper Respiratory Tract Infection | 5 | 4
Rhinitis | 5 | 3
Sinusitis | 3 | <1
General
Fatigue | 5 | 3
Fever | 2 | <1
Musculoskeletal System Disorders
Arthralgia | 2 | 1
Myalgia | 2 | 1

*Adverse reactions reported by at least 2% of patients treated with CELEXA are reported, except for the following adverse reactions which had an incidence on placebo ≥ CELEXA: headache, asthenia, dizziness, constipation, palpitation, vision abnormal, sleep disorder, nervousness, pharyngitis, micturition disorder, back pain.

^1Denominator used was for females only (N=638 CELEXA; N=252 placebo).

^2Primarily ejaculatory delay.

^3Denominator used was for males only (N=425 CELEXA; N=194 placebo).

Dose Dependent Adverse Reactions

The potential relationship between the dosage of CELEXA and the incidence of adverse reactions was examined in a fixed-dose study in patients with MDD receiving placebo or CELEXA 10 mg, 20 mg 40 mg, or 60 mg (1.5 times the maximum recommended dosage). A positive dose response (p<0.05) was revealed for the following adverse reactions: fatigue, impotence, insomnia, increased sweating, somnolence, and yawning.

Male and Female Sexual Dysfunction with SSRIs

Although changes in sexual desire, sexual performance, and sexual satisfaction often occur as manifestations of a psychiatric disorder, they may also be a consequence of SSRI treatment. However, reliable estimates of the incidence and severity of untoward experiences involving sexual desire, performance, and satisfaction are difficult to obtain, in part because patients and healthcare providers may be reluctant to discuss them. Accordingly, estimates of the incidence of untoward sexual experience and performance cited in labeling may underestimate their actual incidence.

Table 4 displays the incidence of sexual adverse reactions reported by at least 2% of male patients taking CELEXA in a pool of placebo-controlled clinical trials in patients with depression.

Table 4: Adverse Reactions (≥2%) Related to Sexual Dysfunction in CELEXA-Treated Male Patients in Pooled Placebo-Controlled Clinical Trials of MDD
 | CELEXA | Placebo
n (males) | 425 (%) | 194 (%)
Abnormal ejaculation (mostly ejaculatory delay) | 6.1 | 1
Decreased libido | 3.8 | <1
Impotence | 2.8 | <1

In female depressed patients receiving CELEXA, the reported incidence of decreased libido and anorgasmia was 1.3% (n=638 females) and 1.1% (n=252 females), respectively.

Weight Changes

Patients treated with CELEXA in controlled trials experienced a weight loss of about 0.5 kg compared to no change for placebo patients.

ECG Changes

In a thorough QT study, CELEXA was found to be associated with a dose-dependent increase in the QTc interval.

Electrocardiograms from CELEXA (N=802) and placebo (N=241) groups were compared with respect to outliers defined as subjects with QTc changes over 60 msec from baseline or absolute values over 500 msec post-dose, and subjects with heart rate increases to over 100 bpm or decreases to less than 50 bpm with a 25% change from baseline (tachycardic or bradycardic outliers, respectively). In the CELEXA group 1.9% of the patients had a change from baseline in QTcF >60 msec compared to 1.2% of the patients in the placebo group. None of the patients in the placebo group had a post-dose QTcF >500 msec compared to 0.5% of the patients in the CELEXA group. The incidence of tachycardic outliers was 0.5% in the CELEXA group and 0.4% in the placebo group. The incidence of bradycardic outliers was 0.9% in the CELEXA group and 0.4% in the placebo group.

Other Adverse Reactions Observed During the Premarketing Evaluation of CELEXA

The following list of adverse reactions does not include reactions that are: 1) included in Table 3 or elsewhere in labeling, 2) for which a drug cause was remote, 3) which were so general as to be uninformative, and those occurring in only one patient.

Adverse reactions are categorized by body system and listed in order of decreasing frequency according to the following definitions: frequent adverse reactions are those occurring on one or more occasions in at least 1/100 patients; infrequent adverse reactions are those occurring in less than 1/100 patients to 1/1000 patients; rare adverse reactions are those occurring in fewer than 1/1000 patients.

Cardiovascular - Frequent: tachycardia, postural hypotension, hypotension. Infrequent: hypertension, bradycardia, edema (extremities), angina pectoris, extrasystoles, cardiac failure, flushing, myocardial infarction, cerebrovascular accident, myocardial ischemia. Rare: transient ischemic attack, phlebitis, atrial fibrillation, cardiac arrest, bundle branch block.

Central and Peripheral Nervous System Disorders - Frequent: paresthesia, migraine. Infrequent: hyperkinesia, vertigo, hypertonia, extrapyramidal disorder, leg cramps, involuntary muscle contractions, hypokinesia, neuralgia, dystonia, abnormal gait, hypoesthesia, ataxia. Rare: abnormal coordination, hyperesthesia, ptosis, stupor.

Endocrine Disorders - Rare: hypothyroidism, goiter, gynecomastia.

Gastrointestinal Disorders - Frequent: saliva increased, flatulence. Infrequent: gastritis, gastroenteritis, stomatitis, eructation, hemorrhoids, dysphagia, teeth grinding, gingivitis, esophagitis. Rare: colitis, gastric ulcer, cholecystitis, cholelithiasis, duodenal ulcer, gastroesophageal reflux, glossitis, jaundice, diverticulitis, rectal hemorrhage, hiccups.

General - Infrequent: hot flushes, rigors, alcohol intolerance, syncope, influenza-like symptoms. Rare: hay fever.

Hemic and Lymphatic Disorders - Infrequent: purpura, anemia, epistaxis, leukocytosis, leucopenia, lymphadenopathy. Rare: pulmonary embolism, granulocytopenia, lymphocytosis, lymphopenia, hypochromic anemia, coagulation disorder, gingival bleeding.

Metabolic and Nutritional Disorders - Frequent: decreased weight, increased weight. Infrequent: increased hepatic enzymes, thirst, dry eyes, increased alkaline phosphatase, abnormal glucose tolerance. Rare: bilirubinemia, hypokalemia, obesity, hypoglycemia, hepatitis, dehydration.

Musculoskeletal System Disorders - Infrequent: arthritis, muscle weakness, skeletal pain. Rare: bursitis, osteoporosis.

Psychiatric Disorders - Frequent: impaired concentration, amnesia, apathy, depression, increased appetite, aggravated depression, suicide attempt, confusion. Infrequent: increased libido, aggressive reaction, paroniria, drug dependence, depersonalization, hallucination, euphoria, psychotic depression, delusion, paranoid reaction, emotional lability, panic reaction, psychosis. Rare: catatonic reaction, melancholia.

Reproductive Disorders/Female* - Frequent: amenorrhea. Infrequent: galactorrhea, breast pain, breast enlargement, vaginal hemorrhage. (*% based on female subjects only: 2955)

Respiratory System Disorders - Frequent: coughing. Infrequent: bronchitis, dyspnea, pneumonia. Rare: asthma, laryngitis, bronchospasm, pneumonitis, sputum increased.

Skin and Appendages Disorders - Frequent: rash, pruritus. Infrequent: photosensitivity reaction, urticaria, acne, skin discoloration, eczema, alopecia, dermatitis, skin dry, psoriasis. Rare: hypertrichosis, decreased sweating, melanosis, keratitis, cellulitis, pruritus ani.

Special Senses - Frequent: abnormal accommodation, taste perversion. Infrequent: tinnitus, conjunctivitis, eye pain. Rare: mydriasis, photophobia, diplopia, abnormal lacrimation, cataract, taste loss.

Urinary System Disorders - Frequent: polyuria. Infrequent: micturition frequency, urinary incontinence, urinary retention, dysuria. Rare: facial edema, hematuria, oliguria, pyelonephritis, renal calculus, renal pain.

6.2 Postmarketing Experience

The following adverse reactions have been identified during postapproval use of citalopram, the racemate, or escitalopram, the S-enantiomer of citalopram. Because these reactions are reported voluntarily from a population of uncertain size, it is not always possible to reliably estimate their frequency or establish a causal relationship to drug exposure.

Blood and Lymphatic System Disorders: hemolytic anemia, thrombocytopenia, prothrombin decreased

Cardiac Disorders: torsade de pointes, ventricular arrhythmia, QT prolonged

Endocrine Disorders: hyperprolactinemia

Eye Disorders: angle-closure glaucoma

Gastrointestinal Disorders: gastrointestinal hemorrhage, pancreatitis

General Disorders and Administrative Site Conditions: withdrawal syndrome

Hepatobiliary Disorders: hepatic necrosis

Immune System Disorders: anaphylaxis, allergic reaction

Musculoskeletal and Connective Tissue Disorders: rhabdomyolysis

Nervous System Disorders: grand mal convulsion(s), myoclonus, choreoathetosis, dyskinesia, akathisia, nystagmus

Pregnancy, Puerperium and Perinatal Conditions: spontaneous abortion

Psychiatric Disorders: delirium

Renal and Urinary Disorders: acute renal failure

Reproductive System and Breast Disorders: priapism

Respiratory, Thoracic and Mediastinal Disorders: anosmia, hyposmia

Skin and Subcutaneous Tissue Disorders: Stevens Johnson Syndrome, epidermal necrolysis, angioedema, erythema multiforme, ecchymosis

Vascular Disorders: thrombosis

7 DRUG INTERACTIONS

Table 5 presents clinically important drug interactions with CELEXA.

Table 5: Clinically Important Drug Interactions with CELEXA
Monoamine Oxidase Inhibitors (MAOIs)
Clinical Impact | Concomitant use of SSRIs, including CELEXA, and MAOIs increases the risk of serotonin syndrome.
Intervention | CELEXA is contraindicated in patients taking MAOIs, including MAOIs such as linezolid or intravenous methylene blue [see Dosage and Administration (2.5), Contraindications (4), Warnings and Precautions (5.3)].
Pimozide
Clinical Impact: | Concomitant use of CELEXA with pimozide increases plasma concentrations of pimozide, a drug with a narrow therapeutic index, and may increase the risk of QT prolongation and/or ventricular arrhythmias compared to use of CELEXA alone [see Clinical Pharmacology (12.2)].
Intervention: | CELEXA is contraindicated in patients taking pimozide [see Contraindications (4), Warnings and Precautions (5.2)].
Drugs that Prolong the QTc Interval
Clinical Impact: | Concomitant use of CELEXA with drugs that prolong QT can cause additional QT prolongation compared to the use of CELEXA alone [see Clinical Pharmacology (12.2)].
Intervention: | Avoid concomitant use of CELEXA with drugs that prolong the QT interval (CELEXA is contraindicated in patients taking pimozide)[see Contraindications (4), Warnings and Precautions (5.2)].
CYP2C19 Inhibitors
Clinical Impact: | Concomitant use of CELEXA with CYP2C19 inhibitors increases the risk of QT prolongation and/or ventricular arrhythmias compared to the use of CELEXA alone [see Clinical Pharmacology (12.2)].
Intervention: | The maximum recommended dosage of CELEXA is 20 mg daily when used concomitantly with a CYP2C19 inhibitor [see Dosage and Administration (2.4), Warnings and Precautions (5.2)].
Other Serotonergic Drugs
Clinical Impact: | Concomitant use of CELEXA and other serotonergic drugs (including other SSRIs, SNRIs, triptans, tricyclic antidepressants, opioids, lithium, buspirone, amphetamines, tryptophan, and St. John's Wort) increases the risk of serotonin syndrome.
Intervention: | Monitor patients for signs and symptoms of serotonin syndrome, particularly during CELEXA initiation and dosage increases. If serotonin syndrome occurs, consider discontinuation of CELEXA and/or concomitant serotonergic drugs [see Warning and Precautions (5.3)].
Drugs That Interfere With Hemostasis (antiplatelet agents and anticoagulants)
Clinical Impact: | Concomitant use of CELEXA and an antiplatelet or anticoagulant may potentiate the risk of bleeding.
Intervention: | Inform patients of the increased risk of bleeding associated with the concomitant use of CELEXA and antiplatelet agents and anticoagulants. For patients taking warfarin, carefully monitor the international normalized ratio [see Warning and Precautions (5.4)].

8 USE IN SPECIFIC POPULATIONS

8.1 Pregnancy

Pregnancy Exposure Registry

There is a pregnancy exposure registry that monitors pregnancy outcomes in women exposed to antidepressants during pregnancy. Healthcare providers are encouraged to advise patients to register by calling the National Pregnancy Registry for Antidepressants at 1-844-405-6185 or visiting online at

https://womensmentalhealth.org/research/pregnancyregistry/antidepressants.

Risk Summary

Based on data from published observational studies, exposure to SSRIs, particularly in the month before delivery, has been associated with a less than 2-fold increase in the risk of postpartum hemorrhage [see Warnings and Precautions (5.4) and Clinical Considerations].

Available data from published epidemiologic studies and postmarketing reports with citalopram use in pregnancy have not established an increased risk of major birth defects or miscarriage. Published studies demonstrated that citalopram levels in both cord blood and amniotic fluid are similar to those observed in maternal serum. There are risks of persistent pulmonary hypertension of the newborn (PPHN) (see Data) and/or poor neonatal adaptation with exposure to selective serotonin reuptake inhibitors (SSRIs), including CELEXA, during pregnancy. There also are risks associated with untreated depression in pregnancy (see Clinical Considerations).

In animal reproduction studies, citalopram caused adverse embryo/fetal effects at doses that caused maternal toxicity (see Data).

The estimated background risk of major birth defects and miscarriage for the indicated population is unknown. All pregnancies have a background risk of birth defect, loss, or other adverse outcomes. In the U.S. general population, the estimated background risk of major birth defects and miscarriage in the clinically recognized pregnancies is 2% to 4% and 15% to 20%, respectively.

Clinical Considerations

Disease-Associated Maternal and/or Embryo/Fetal Risk

Women who discontinue antidepressants during pregnancy are more likely to experience a relapse of major depression than women who continue antidepressants. This finding is from a prospective longitudinal study of 201 pregnant women with a history of major depressive disorder who were euthymic and taking antidepressants at the beginning of pregnancy. Consider the risk of untreated depression when discontinuing or changing treatment with antidepressant medication during pregnancy and postpartum.

Maternal Adverse Reactions

Use of CELEXA in the month before delivery may be associated with an increased risk of postpartum hemorrhage [see Warnings and Precautions (5.4)].

Fetal/Neonatal Adverse Reactions

Neonates exposed to CELEXA and other SSRIs late in third trimester have developed complications requiring prolonged hospitalization, respiratory support, and tube feeding. Such complications can arise immediately upon delivery. Reported clinical findings have included respiratory distress, cyanosis, apnea, seizures, temperature instability, feeding difficulty, vomiting, hypoglycemia, hypotonia, hypertonia, hyperreflexia, tremor, jitteriness, irritability, and constant crying. These findings are consistent with either a direct toxic effect of SSRIs or possibly, a drug discontinuation syndrome. It should be noted that, in some cases, the clinical picture is consistent with serotonin syndrome [see Warnings and Precautions (5.3)].

Data

Human Data

Exposure during late pregnancy to SSRIs may have an increased risk for persistent pulmonary hypertension of the newborn (PPHN). PPHN occurs in 1- 2 per 1,000 live births in the general population and is associated with substantial neonatal morbidity and mortality.

Animal Data

Citalopram was administered orally to pregnant rats during the period of organogenesis at doses of 32, 56, and 112 mg/kg/day, which are approximately 8, 14, and 27 times the Maximum Recommended Human Dose (MRHD) of 40 mg, based on mg/m^2 body surface area. Citalopram caused maternal toxicity of CNS clinical signs and decreased weight gain at 112 mg/kg/day, which is 27 times the MRHD. At this maternally toxic dose, citalopram decreased embryo/fetal growth and survival and increased fetal abnormalities (including cardiovascular and skeletal defects). The no observed adverse effect level (NOAEL) for maternal and embryofetal toxicity is 56 mg/kg/day, which is approximately 14 times the MRHD.

Citalopram was administered orally to pregnant rabbits during the period of organogenesis at doses up to 16 mg/kg/day, which is approximately 8 times the MRHD of 40 mg, based on mg/m^2 body surface area. No maternal or embryofetal toxicity was observed. The NOAEL for maternal and embryofetal toxicity is 16 mg/kg/day, which is approximately 8 times the MRHD.

Citalopram was administered orally to pregnant rats during late gestation and lactation periods at doses of 4.8, 12.8, and 32 mg/kg/day, which are approximately 1, 3, and 8 times the MRHD of 40 mg, based on mg/m^2 body surface area. Citalopram increased offspring mortality during the first 4 days of birth and decreased offspring growth at 32 mg/kg/day, which is approximately 8 times the MRHD. The NOAEL for developmental toxicity is 12.8 mg/kg/day, which is approximately 3 times the MRHD. In a separate study, similar effects on offspring mortality and growth were seen when dams were treated throughout gestation and early lactation at doses ≥ 24 mg/kg/day, which is approximately 6 times the MRHD. A NOAEL was not determined in that study.

8.2 Lactation

Risk Summary

Data from the published literature report the presence of citalopram in human milk at relative infant doses ranging between 0.7 to 9.4% of the maternal weight-adjusted dosage and a milk/plasma ratio ranging between 0.78 to 4.3. There are reports of breastfed infants exposed to citalopram experiencing irritability, restlessness, excessive somnolence, decreased feeding, and weight loss (see Clinical Considerations). There is no information about effects of citalopram on milk production.

The developmental and health benefits of breastfeeding should be considered along with the mother’s clinical need for CELEXA and any potential adverse effects on the breastfed child from CELEXA or from the underlying maternal condition.

Clinical Considerations

Monitor breastfeeding infants for adverse reactions, such as irritability, restlessness, excessive somnolence, decreased feeding, and weight loss.

8.4 Pediatric Use

The safety and effectiveness of CELEXA have not been established in pediatric patients. Two placebo-controlled trials in 407 pediatric patients with MDD have been conducted with CELEXA, and the data were not sufficient to support use in pediatric patients.

Antidepressants increase the risk of suicidal thoughts and behaviors in pediatric patients [see Boxed Warning, Warnings and Precautions (5.1)]. Decreased appetite and weight loss have been observed in association with the use of SSRIs in pediatric patients.

8.5 Geriatric Use

Of 4422 patients in clinical studies of CELEXA, 1357 were 60 and over, 1034 were 65 and over, and 457 were 75 and over. In two pharmacokinetic studies, citalopram AUC was increased by 23% and 30%, respectively, in subjects ≥ 60 years of age as compared to younger subjects, and its half-life was increased by 30% and 50%, respectively [see Clinical Pharmacology (12.3)]. Therefore, the maximum recommended dosage in patients 60 years of age and older is lower than younger patients [see Dosage and Administration (2.3), Warnings and Precautions (5.2)].

SSRIs, including CELEXA, have been associated with cases of clinically significant hyponatremia in elderly patients, who may be at greater risk for this adverse reaction [see Warnings and Precautions (5.9)].

8.6 Hepatic Impairment

Increased citalopram exposure occurs in patients with hepatic impairment. The maximum recommended dosage of CELEXA is lower in patients with hepatic impairment [see Dosage and Administration (2.3), Clinical Pharmacology (12.3)].

9 DRUG ABUSE AND DEPENDENCE

9.1 Controlled Substance

CELEXA (citalopram HBr) is not a controlled substance.

9.2 Abuse

Animal studies suggest that the abuse liability of CELEXA is low. CELEXA has not been systematically studied in humans for its potential for abuse, tolerance, or physical dependence. The premarketing clinical experience with CELEXA did not reveal any drug-seeking behavior. However, these observations were not systematic and it is not possible to predict, on the basis of this limited experience, the extent to which a CNS-active drug will be misused, diverted, and/or abused once marketed. Consequently, health care providers should carefully evaluate CELEXA patients for history of drug abuse and follow such patients closely, observing them for signs of misuse or abuse (e.g., development of tolerance, incrementations of dose, drug-seeking behavior).

10 OVERDOSAGE

The following have been reported with CELEXA tablet overdosage:

- Seizures, which may be delayed, and altered mental status including coma.
- Cardiovascular toxicity, which may be delayed, including QRS and QTc interval prolongation, wide complex tachyarrhythmias, and torsade de pointes. Hypertension most commonly seen, but rarely can see hypotension alone or with co‐ingestants including alcohol.
- Serotonin syndrome (patients with a multiple drug overdosage with other proserotonergic drugs may have a higher risk).

Prolonged cardiac monitoring is recommended in CELEXA overdosage ingestions due to the arrhythmia risk. Gastrointestinal decontamination with activated charcoal should be considered in patients who present early after a CELEXA overdose. Consider contacting a Poison Center (1‐800‐221‐2222) or a medical toxicologist for additional overdosage management recommendations.

11 DESCRIPTION

CELEXA contains citalopram, a selective serotonin reuptake inhibitor (SSRI). Citalopram hydrobromide is a racemic bicyclic phthalane structure and is designated (±)-1-(3-dimethylaminopropyl)-1-(4-fluorophenyl)-1,3-dihydroisobenzofuran-5-carbonitrile hydrobromide with the following structural formula:

The molecular formula is C20H22BrFN2O and its molecular weight is 405.35.

Citalopram hydrobromide occurs as a fine, white to off-white powder. Citalopram hydrobromide is sparingly soluble in water and soluble in ethanol.

CELEXA tablets are for oral administration and are available as film-coated oval tablets. The strengths reflect citalopram base equivalent content. The 10 mg, 20 mg, and 40 mg strength tablets contain 12.49 mg, 24.98 mg, and 49.96 mg of citalopram hydrobromide, respectively. The 20 mg and 40 mg tablets are scored.

Inactive ingredients: copolyvidone, corn starch, crosscarmellose sodium, glycerin, lactose monohydrate, magnesium stearate, hypromellose, microcrystalline cellulose, polyethylene glycol, and titanium dioxide. Iron oxides are used as coloring agents in the beige (10 mg) and pink (20 mg) tablets.

12 CLINICAL PHARMACOLOGY

12.1 Mechanism of Action

The mechanism of action of citalopram is unclear, but is presumed to be related to potentiation of serotonergic activity in the central nervous system (CNS) resulting from its inhibition of CNS neuronal reuptake of serotonin (5-HT).

12.2 Pharmacodynamics

In vitro and in vivo studies in animals suggest that citalopram is a selective serotonin reuptake inhibitor (SSRI) with minimal effects on norepinephrine (NE) and dopamine (DA) neuronal reuptake.

Citalopram has no or very low affinity for 5-HT1A, 5-HT2A, dopamine D1 and D2, α1-, α2-, and β-adrenergic, histamine H1, gamma aminobutyric acid (GABA), muscarinic cholinergic, and benzodiazepine receptors.

Cardiac Electrophysiology

Individually corrected QTc (QTcNi) interval was evaluated in a randomized, placebo and active (moxifloxacin 400 mg) controlled cross-over, escalating multiple-dose study in 119 healthy subjects. The maximum mean (upper bound of the 95% one-sided confidence interval) difference from placebo were 8.5 (10.8) and 18.5 (21.0) msec for 20 mg and 60 mg (1.5 times the maximum recommended dosage) citalopram, respectively. Based on the established exposure-response relationship, the predicted QTcNi change from placebo (upper bound of the 95% one-sided confidence interval) under the Cmax for the dose of 40 mg is 12.6 (14.3) msec [see Warnings and Precautions (5.2)].

12.3 Pharmacokinetics

The single- and multiple-dose pharmacokinetics of citalopram are linear and dose-proportional in a dose range of 10 to 40 mg/day. Biotransformation of citalopram is mainly hepatic, with a mean terminal half-life of about 35 hours. With once daily dosing, steady state plasma concentrations are achieved within approximately one week. At steady state, the extent of accumulation of citalopram in plasma, based on the half-life, is expected to be 2.5 times the plasma concentrations observed after a single dose.

Absorption

Following a single oral dose (40 mg tablet) of citalopram, peak blood levels occur at about 4 hours. The absolute bioavailability of citalopram was about 80% relative to an intravenous dose, and absorption is not affected by food.

Distribution

The volume of distribution of citalopram is about 12 L/kg and the binding of citalopram (CT), demethylcitalopram (DCT) and didemethylcitalopram (DDCT) to human plasma proteins is about 80%.

Elimination

Metabolism

Citalopram is metabolized to demethylcitalopram (DCT), didemethylcitalopram (DDCT), citalopram-N-oxide, and a deaminated propionic acid derivative. In humans, unchanged citalopram is the predominant compound in plasma. At steady state, the concentrations of citalopram's metabolites, DCT and DDCT, in plasma are approximately one-half and one-tenth, respectively, that of the parent drug. In vitro studies show that citalopram is at least 8 times more potent than its metabolites in the inhibition of serotonin reuptake, suggesting that the metabolites evaluated do not likely contribute significantly to the antidepressant actions of citalopram.

In vitro studies using human liver microsomes indicated that CYP3A4 and CYP2C19 are the primary isozymes involved in the N-demethylation of citalopram.

Excretion

Following intravenous administrations of citalopram, the fraction of drug recovered in the urine as citalopram and DCT was about 10% and 5%, respectively. The systemic clearance of citalopram was 330 mL/min, with approximately 20% of that due to renal clearance.

Specific Populations

Geriatric Patients

Citalopram pharmacokinetics in subjects ≥ 60 years of age were compared to younger subjects in two normal volunteer studies. In a single-dose study, citalopram AUC and half-life were increased in the subjects ≥ 60 years old by 30% and 50%, respectively, whereas in a multiple-dose study they were increased by 23% and 30%, respectively[see Dosage and Administration (2.3), Warnings and Precautions (5.2), Use in Specific Populations (8.5)].

Male and Female Patients

In three pharmacokinetic studies (total N=32), citalopram AUC in women was one and a half to two times that in men. This difference was not observed in five other pharmacokinetic studies (total N=114). In clinical studies, no differences in steady state serum citalopram levels were seen between men (N=237) and women (N=388). There were no gender differences in the pharmacokinetics of DCT and DDCT.

Patients with Hepatic Impairment

Citalopram oral clearance was reduced by 37% and half-life was doubled in patients with reduced hepatic function compared to normal subjects [see Dosage and Administration (2.3), Warnings and Precautions (5.2), Use in Specific Populations (8.6)].

Patients with Renal Impairment

In patients with mild to moderate renal impairment, oral clearance of citalopram was reduced by 17% compared to normal subjects. No adjustment of dosage for such patients is recommended. No information is available about the pharmacokinetics of citalopram in patients with severe renal impairment (creatinine clearance < 20 mL/min).

CYP2C19 poor metabolizers

In CYP2C19 poor metabolizers, citalopram steady state Cmax and AUC was increased by 68% and 107%, respectively [see Dosage and Administration (2.3),Warnings and Precautions (5.2)].

CYP2D6 poor metabolizers

Citalopram steady state levels were not significantly different in poor metabolizers and extensive metabolizers of CYP2D6.

Drug Interaction Studies

In vitro enzyme inhibition data did not reveal an inhibitory effect of citalopram on CYP3A4, -2C9, or -2E1, but did suggest that it is a weak inhibitor of CYP1A2, -2D6, and -2C19. Citalopram would be expected to have little inhibitory effect on in vivo metabolism mediated by these enzymes. However, in vivo data to address this question are limited.

CYP3A4 and CYP2C19 Inhibitors

Since CYP3A4 and CYP2C19 are the primary enzymes involved in the metabolism of citalopram, it is expected that potent inhibitors of CYP3A4 (e.g., ketoconazole, itraconazole, and macrolide antibiotics) and inhibitors of CYP2C19 (e.g., omeprazole, cimetidine) might decrease the clearance of citalopram. However, coadministration of citalopram and the potent CYP3A4 inhibitor ketoconazole did not significantly affect the pharmacokinetics of citalopram. 20 mg/day is the maximum recommended citalopram dose in patients taking concomitant cimetidine or another CYP2C19 inhibitor, because of the risk of QT prolongation [see Dosage and Administration (2.2), Warnings and Precautions (5.2)].

Cimetidine

In subjects who had received 21 days of 40 mg/day CELEXA, combined administration of 400 mg twice a day cimetidine for 8 days resulted in an increase in citalopram AUC and Cmax of 43% and 39%, respectively [see Dosage and Administration (4),Warnings and Precautions (5.2), Drug Interactions (7)].

CYP2D6 Inhibitors

Coadministration of a drug that inhibits CYP2D6 with citalopram is unlikely to have clinically significant effects on citalopram metabolism, based on the study results in CYP2D6 poor metabolizers.

Digoxin

In subjects who had received 21 days of 40 mg/day CELEXA, combined administration of CELEXA and digoxin (single dose of 1 mg) did not significantly affect the pharmacokinetics of either citalopram or digoxin.

Lithium

Coadministration of CELEXA (40 mg/day for 10 days) and lithium (30 mmol/day for 5 days) had no significant effect on the pharmacokinetics of citalopram or lithium.

Pimozide

In a controlled study, a single dose of pimozide 2 mg co-administered with citalopram 40 mg given once daily for 11 days was associated with a mean increase in QTc values of approximately 10 msec compared to pimozide given alone. Citalopram did not alter the mean AUC or Cmax of pimozide. The mechanism of this pharmacodynamic interaction is not known [see Contraindications (4), Warnings and Precautions (5.2)].

Theophylline

Combined administration of CELEXA (40 mg/day for 21 days) and the CYP1A2 substrate theophylline (single dose of 300 mg) did not affect the pharmacokinetics of theophylline. The effect of theophylline on the pharmacokinetics of citalopram was not evaluated.

Warfarin

Administration of 40 mg/day CELEXA for 21 days did not affect the pharmacokinetics of warfarin, a CYP3A4 substrate. Prothrombin time was increased by 5%, the clinical significance of which is unknown.

Carbamazepine

Combined administration of CELEXA (40 mg/day for 14 days) and carbamazepine (titrated to 400 mg/day for 35 days) did not significantly affect the pharmacokinetics of carbamazepine, a CYP3A4 substrate. Although trough citalopram plasma levels were unaffected, given the enzyme-inducing properties of carbamazepine, the possibility that carbamazepine might increase the clearance of citalopram should be considered if the two drugs are coadministered.

Triazolam

Combined administration of CELEXA (titrated to 40 mg/day for 28 days) and the CYP3A4 substrate triazolam (single dose of 0.25 mg) did not significantly affect the pharmacokinetics of either citalopram or triazolam.

Ketoconazole

Combined administration of CELEXA (40 mg) and ketoconazole (200 mg) decreased the Cmax and AUC of ketoconazole by 21% and 10%, respectively, and did not significantly affect the pharmacokinetics of citalopram.

Metoprolol

Administration of 40 mg/day CELEXA for 22 days resulted in a two-fold increase in the plasma levels of the beta-adrenergic blocker metoprolol. Increased metoprolol plasma levels have been associated with decreased cardioselectivity. Coadministration of CELEXA and metoprolol had no clinically significant effects on blood pressure or heart rate.

Imipramine and Other Tricyclic Antidepressants (TCAs)

In vitro studies suggest that citalopram is a relatively weak inhibitor of CYP2D6. Coadministration of CELEXA (40 mg/day for 10 days) with the TCA imipramine (single dose of 100 mg), a substrate for CYP2D6, did not significantly affect the plasma concentrations of imipramine or citalopram. However, the concentration of the imipramine metabolite desipramine was increased by approximately 50%. The clinical significance of the desipramine change is unknown.

13 NONCLINICAL TOXICOLOGY

13.1 Carcinogenesis, Mutagenesis, Impairment of Fertility

Carcinogenesis

Citalopram increased the incidence of small intestine carcinoma in rats treated for 24 months at doses of 8 and 24 mg/kg/day in the diet, which are approximately 2 and 6 times the Maximum Recommended Human Dose (MRHD) of 40 mg, respectively, based on mg/m^2 body surface area. A no-effect level (NOEL) for this finding was not established.

Citalopram did not increase the incidence of tumors in mice treated for 18 months at doses up 240 mg/kg/day in the diet, which is approximately 30 times the MRDH of 40 mg based on mg/m^2 body surface area.

Mutagenesis

Citalopram was mutagenic in the in vitro bacterial reverse mutation assay (Ames test) in 2 of 5 bacterial strains (Salmonella TA98 and TA1537) in the absence of metabolic activation. It was clastogenic in the in vitro Chinese hamster lung cell assay for chromosomal aberrations in the presence and absence of metabolic activation. Citalopram was not mutagenic in the in vitro mammalian forward gene mutation assay (HPRT) in mouse lymphoma cells or in in vitro/in vivo unscheduled DNA synthesis (UDS) assay in rat liver. It was not clastogenic in the in vitro chromosomal aberration assay in human lymphocytes or in two in vivo mouse micronucleus assays.

Impairment of Fertility

Citalopram was administered orally to female and male rats at doses of 32, 48, and 72 mg/kg/day prior to and throughout mating and continuing to gestation. These doses are approximately 8, 12, and 17 times the MRHD of 40 mg based on mg/m^2 body surface area. Mating and fertility were decreased at doses ≥ 32 mg/kg/day, which is approximately 8 times the MRHD. Gestation duration was increased at 48 mg/kg/day, which is approximately 12 times the MRHD.

13.2 Animal Toxicology and/or Pharmacology

Retinal Changes in Rats

Pathologic changes (degeneration/atrophy) were observed in the retinas of albino rats in the 2-year carcinogenicity study with citalopram. There was an increase in both incidence and severity of retinal pathology in both male and female rats receiving 80 mg/kg/day, which is approximately 19 times the MRHD of 40 mg based on mg/m^2 body surface area. Similar findings were not present in rats treated for two years at the dose of 24 mg/kg/day, in mice treated for 18 months at doses up to 240 mg/kg/day, or in dogs treated for one year at doses up to 20 mg/kg/day, which are approximately 6, 29, and 17 times the MRHD, respectively, based on mg/m^2 body surface area.

Additional studies to investigate the mechanism for this pathology have not been performed, and the potential significance of this effect in humans has not been established.

14 CLINICAL STUDIES

The efficacy of CELEXA as a treatment for major depressive disorder was established in two placebo-controlled studies (of 4 to 6 weeks duration) in adult outpatients (ages 18-66) meeting DSM-III or DSM-III-R criteria for major depressive disorder (MDD) (Studies 1 and 2).

Study 1, a 6-week trial in which patients received fixed CELEXA doses of 10 mg, 20 mg, 40 mg, and 60 mg daily, showed that CELEXA 40 daily and 60 mg daily (1.5 times the maximum recommended daily dosage) was effective as measured by the Hamilton Depression Rating Scale (HAMD) total score, the primary efficacy endpoint. The HAMD-17 is a 17-item, clinician-rated scale used to assess severity of depressive symptoms. Scores on the HAMD-17 range from 0 to 52, with higher scores indicating more severe depression. This study showed no clear effect of the 10 mg and 20 mg daily doses, and the 60 mg daily dose was not more effective than the 40 mg daily dose. Due to the risk of QTc prolongation and ventricular arrhythmias, the maximum recommended dosage of CELEXA is 40 mg once daily.

In study 2, a 4-week, placebo-controlled trial in patients with MDD, the initial dose was 20 mg daily, followed by titration to the maximum tolerated dose or a maximum dose of 80 mg daily (2 times the maximum recommended daily dosage). Patients treated with CELEXA showed statistically significantly greater improvement than placebo patients on the HAMD total score, the primary efficacy endpoint. In three additional placebo-controlled trials in patients with MDD, the difference in response to treatment between patients receiving CELEXA and patients receiving placebo was not statistically significant.

In two long-term studies, patients with MDD who had responded to CELEXA during an initial 6 or 8 weeks of acute treatment were randomized to continuation of CELEXA or placebo. In one study, patients received fixed doses of CELEXA 20 mg or 40 mg daily and in the second study, patients received flexible doses of CELEXA 20 mg daily to 60 mg daily (1.5 times the maximum recommended daily dosage). In both studies, patients receiving continued CELEXA treatment experienced statistically significantly lower relapse rates over the subsequent 6 months compared to those receiving placebo. In the fixed-dose study, the decreased rate of depression relapse was similar in patients receiving 20 mg or 40 mg daily of CELEXA. Due to the risk of QTc prolongation and ventricular arrhythmias, the maximum recommended dosage of CELEXA is 40 mg once daily.

Analyses of the relationship between treatment outcome and age, gender, and race did not suggest any differential responsiveness on the basis of these patient characteristics.

16 HOW SUPPLIED/STORAGE AND HANDLING

CELEXA (citalopram) tablets are supplied as follows:

Strength | Color/Shape | Engraved Descriptors | Package Configuration | NDC Number
10 mg | Beige, oval | “FP” on one side and “10 mg” on other side. | Bottle of 100 | NDC # 0456-4010-01
20 mg | Pink, oval | Scored with “F” on left side of score line and "P" on right side of score line; “20 mg” on non-scored side | Bottle of 100 | NDC # 0456-4020-01
 |  |  | 10 x 10 unit dose | NDC # 0456-4020-63
40 mg | White, oval | Scored with “F” on left side of score line and "P" on right side of score line; “40 mg” on non-scored side | Bottle of 100 | NDC # 0456-4040-01
 |  |  | 10 x 10 unit dose | NDC # 0456-4040-63

Storage and Handling

CELEXA tablets should be stored at 20-25°C (68 to 77°F); excursions permitted between 15 and 30°C (59-86°F) [see USP Controlled Room Temperature].

17 PATIENT COUNSELING INFORMATION

Advise the patient to read the FDA-approved patient labeling (Medication Guide).

Suicidal Thoughts and Behaviors

Advise patients and caregivers to look for the emergence of suicidality, especially early during treatment and when the dosage is adjusted up or down, and instruct them to report such symptoms to the healthcare provider [see Boxed Warning, Warnings and Precautions (5.1)].

QT Prolongation and Torsade de Pointes

Advise patients to consult their health care provider immediately if they feel faint, lose consciousness, or have heart palpitations. Instruct patients to inform their health care provider that they are taking CELEXA before taking any new medications [see Warnings and Precautions (5.2), Drug Interactions (7)].

Serotonin Syndrome

Caution patients about the risk of serotonin syndrome, particularly with the concomitant use of CELEXA with other serotonergic drugs including triptans, tricyclic antidepressants, opioids, lithium, tryptophan, buspirone, amphetamines, St. John’s Wort, and with drugs that impair metabolism of serotonin (in particular, MAOIs, both those intended to treat psychiatric disorders and also others, such as linezolid). Instruct patients to contact their health care provider or report to the emergency room if they experience signs or symptoms of serotonin syndrome [see Warnings and Precautions (5.3), Drug Interactions (7)].

Increased Risk of Bleeding

Inform patients about the concomitant use of CELEXA with aspirin, NSAIDs, other antiplatelet drugs, warfarin, or other anticoagulants because the combined use has been associated with an increased risk of bleeding. Advise patients to inform their health care providers if they are taking or planning to take any prescription or over-the counter medications that increase the risk of bleeding [see Warnings and Precautions (5.4)].

Activation of Mania or Hypomania

Advise patients and their caregivers to observe for signs of activation of mania/hypomania and instruct them to report such symptoms to the healthcare provider [see Warnings and Precautions (5.5)].

Discontinuation Syndrome

Advise patients not to abruptly discontinue CELEXA and to discuss any tapering regimen with their healthcare provider. Inform patients that adverse reactions can occur when CELEXA is discontinued [See Warnings and Precautions (5.6)].

Sexual Dysfunction

Advise patients that use of CELEXA may cause symptoms of sexual dysfunction in both male and female patients. Inform patients that they should discuss any changes in sexual function and potential management strategies with their healthcare provider [see Warnings and Precautions (5.10)].

Pregnancy

- Advise patients to notify their healthcare provider if they become pregnant or intend to become pregnant during treatment with CELEXA [see Use in Specific Populations (8.1)].
- Advise patients that CELEXA use late in pregnancy may lead to an increased risk for neonatal complications requiring prolonged hospitalization, respiratory support, tube feeding, and/or persistent pulmonary hypertension of the newborn (PPHN) [see Use in Specific Populations (8.1)].
- Advise women that there is a pregnancy exposure registry that monitors pregnancy outcomes in women exposed to citalopram during pregnancy [see Use in Specific Populations (8.1)].

Lactation

Advise breastfeeding women to monitor infants for excess sedation, restlessness, agitation, poor feeding and poor weight gain and to seek medical care if they notice these signs [see Use in Specific Populations (8.2)].

Distributed by:

AbbVie Inc.
1 N Waukegan Rd.
North Chicago, IL 60064
Licensed from H. Lundbeck A/S

© 2023 AbbVie. All rights reserved.

CELEXA and its design are trademarks of H. Lundbeck A/S, used under license by AbbVie.

20081725

MEDICATION GUIDE
CELEXA® (Suh-leks-uh)
(citalopram)
Tablets, for oral use

What is the most important information I should know about CELEXA?
CELEXA may cause serious side effects, including:

- Increased risk of suicidal thoughts and actions. CELEXA and other antidepressant medicines may increase suicidal thoughts and actions in some children, adolescents, and young adults especially within the first few months of treatment or when the dose is changed. CELEXA is not for use in children.

- Depression and other mental illnesses are the most important causes of suicidal thoughts and actions.

How can I watch for and try to prevent suicidal thoughts and actions in myself or a family member?

- Pay close attention to any changes, especially sudden changes in mood, behavior, thoughts, or feelings, or if you develop suicidal thoughts or actions. This is very important when an antidepressant medicine is started or when the dose is changed.
- Call your healthcare provider right away to report new or sudden changes in mood, behavior, thoughts, or feelings.
- Keep all follow-up visits with your healthcare provider as scheduled. Call your healthcare provider between visits as needed, especially if you have concerns about symptoms.

Call your healthcare provider or get emergency medical help right away if you or your family member have any of the following symptoms, especially if they are new, worse, or worry you:

- thoughts about suicide or dying
- new or worse depression
- feeling very agitated or restless
- trouble sleeping (insomnia)
- acting aggressive, being angry, or violent
- an extreme increase in activity or talking (mania)

- attempts to commit suicide
- new or worse anxiety
- acting on dangerous impulses
- panic attacks
- new or worse irritability
- other unusual changes in behavior or mood

What is CELEXA?
CELEXA is a prescription medicine used to treat a certain type of depression called Major Depressive Disorder (MDD) in adults.
It is not known if CELEXA is safe and effective for use in children.

Who should not take CELEXA?
Do not take CELEXA if you:

- take a Monoamine Oxidase Inhibitor (MAOI)
- have stopped taking an MAOI in the last 14 days
- are being treated with the antibiotic linezolid or intravenous methylene blue
- take pimozide
- are allergic to citalopram or any of the ingredients in CELEXA. See the end of this Medication Guide for a complete list of ingredients in CELEXA.

Ask your healthcare provider or pharmacist if you are not sure if you take an MAOI, including MAOIs such as linezolid or intravenous methylene blue.
Do not start taking an MAOI for at least 14 days after you stop treatment with CELEXA.

Before taking CELEXA, tell your healthcare provider about all your medical conditions, including if you:

- have or have a family history of suicide, depression, bipolar disorder, mania or hypomania
- have an abnormal heart rhythm called QT prolongation
- have or had heart problems, including a heart attack, heart failure, abnormal heart rhythm, or long QT syndrome
- have low potassium, magnesium, or sodium levels in your blood
- have or had bleeding problems
- have or had seizures (convulsions)
- have high pressure in the eye (glaucoma)
- have or had kidney or liver problems
- are pregnant or plan to become pregnant. CELEXA may harm your unborn baby. Taking CELEXA late in pregnancy may lead to an increased risk of certain problems in your newborn. Talk to your healthcare provider about the risks and benefits of treating depression during pregnancy.
  ◦ Tell your healthcare provider right away if you become pregnant or think you may be pregnant during treatment with CELEXA.
  ◦ There is a pregnancy registry for females who are exposed to CELEXA during pregnancy. The purpose of the registry is to collect information about the health of females exposed to CELEXA and their baby. If you become pregnant during treatment with CELEXA, talk to your healthcare provider about registering with the National Pregnancy Registry for Antidepressants. You can register by calling 1-844-405-6185 or visiting online at https://womensmentalhealth.org/research/pregnancyregistry/antidepressants.

- are breastfeeding or plan to breastfeed. It is not known if CELEXA passes into your breast milk. Talk to your healthcare provider about the best way to feed your baby during treatment with CELEXA.
  ◦ If you breastfeed during treatment with CELEXA, call your healthcare provider right away if your baby develops sleepiness or fussiness, or is not feeding or gaining weight well.

Tell your healthcare provider about all the medicines you take, including prescription and over-the-counter medicines, vitamins, and herbal supplements.
CELEXA and other medicines may affect each other causing possible serious side effects. CELEXA may affect the way other medicines work and other medicines may affect the way CELEXA works.
Especially tell your healthcare provider if you take:

- medicines used to treat migraine headaches known as triptans
- tricyclic antidepressants
- lithium
- tramadol, fentanyl, meperidine, methadone, or other opioids
- tryptophan
- buspirone
- amphetamines
- St. John’s Wort
- medicines that can affect blood clotting such as aspirin, nonsteroidal anti-inflammatory drugs (NSAIDs) and warfarin
- diuretics
- methadone
- gatifloxacin or moxifloxacin
- medicines used to control your heart rate or rhythm (antiarrhythmics)
- medicines used to treat mood, anxiety, psychotic or thought disorders, including selective serotonin reuptake inhibitors (SSRIs) and serotonin norepinephrine reuptake inhibitors (SNRIs)

Ask your healthcare provider if you are not sure if you are taking any of these medicines. Your healthcare provider can tell you if it is safe to take CELEXA with your other medicines.
Do not start or stop any other medicines during treatment with CELEXA without talking to your healthcare provider first. Stopping CELEXA suddenly may cause you to have serious side effects. See, “What are the possible side effects of CELEXA?”
Know the medicines you take. Keep a list of them to show to your healthcare provider and pharmacist when you get a new medicine.

How should I take CELEXA?

- Take CELEXA exactly as your healthcare provider tells you to take it. Do not change your dose or stop taking CELEXA without first talking to your healthcare provider.
- Your healthcare provider may need to change the dose of CELEXA until it is the right dose for you.
- Take CELEXA 1 time each day with or without food.
- If you take too much CELEXA, call your healthcare provider or poison control center at 1-800-222-1222, or go to the nearest hospital emergency room right away.

What are the possible side effects of CELEXA?
CELEXA may cause serious side effects, including:

- See, “What is the most important information I should know about CELEXA?”
- Heart rhythm problems. CELEXA may cause a serious change in your heartbeat (a fast or irregular heartbeat) that may cause death. Tell your healthcare provider right away if you feel faint or pass out, or if you have a change in your heart beat.
- Serotonin syndrome. Taking CELEXA can cause a potentially life-threatening problem called serotonin syndrome. The risk of developing serotonin syndrome is increased when CELEXA is taken with certain other medicines. See, “Who should not take CELEXA?” Call your healthcare provider or go to the nearest hospital emergency room right away if you have any of the following signs and symptoms of serotonin syndrome:

- agitation
- confusion
- fast heart beat
- dizziness
- flushing
- tremors, stiff muscles, or muscle twitching
- seizures

- seeing or hearing things that are not real (hallucinations)
- coma
- blood pressure changes
- sweating
- high body temperature (hyperthermia)
- loss of coordination
- nausea, vomiting, diarrhea

- Increased risk of bleeding. Taking CELEXA with aspirin, non-steroidal anti-inflammatory drugs (NSAIDs), warfarin or blood thinners may add to this risk. Tell your healthcare provider right away about any unusual bleeding or bruising.
- Manic episodes. Manic episodes may happen in people with bipolar disorder who take CELEXA. Symptoms may include:

- greatly increased energy
- racing thoughts
- unusually grand ideas
- talking more or faster than usual

- severe trouble sleeping
- reckless behavior
- excessive happiness or irritability

- Discontinuation syndrome. Suddenly stopping CELEXA may cause you to have serious side effects. Your healthcare provider may want to decrease your dose slowly. Symptoms may include:

- nausea
- changes in your mood
- irritability and agitation
- dizziness
- electric shock sensation (paresthesia)
- anxiety
- confusion

- sweating
- headache
- tiredness
- problems sleeping
- hypomania
- ringing in your ears (tinnitus)
- seizures

- Seizures (convulsions).
- Eye problems (angle-closure glaucoma). Many antidepressant medicines, including CELEXA, may cause a certain type of eye problem called angle-closure glaucoma. Call your healthcare provider if you have changes in your vision or eye pain.
- Low sodium levels in your blood (hyponatremia). Low sodium levels in your blood may be serious and may cause death. Elderly people may be at greater risk for this. Tell your healthcare provider right away if you develop any signs or symptoms of low sodium levels in your blood during treatment with CELEXA. Signs and symptoms of low sodium levels in your blood may include:

- headache
- memory changes
- weakness and unsteadiness on your feet which can lead to falls

- difficulty concentrating
- confusion

In severe or more sudden cases, signs and symptoms include:

- hallucinations (seeing or hearing things that are not real)
- seizures
- stopping breathing

- fainting
- coma
- death

- Sexual problems (dysfunction). Taking selective serotonin reuptake inhibitors (SSRIs), including CELEXA, may cause sexual problems.

Symptoms in males may include:

- Delayed ejaculation or inability to have an ejaculation
- Decreased sex drive
- Problems getting or keeping an erection

Symptoms in females may include:

- Decreased sex drive
- Delayed orgasm or inability to have an orgasm

Talk to your healthcare provider if you develop any changes in your sexual function or if you have any questions or concerns about sexual problems during treatment with CELEXA. There may be treatments your healthcare provider can suggest.
The most common side effect of CELEXA is delayed ejaculation.
These are not all the possible side effects of CELEXA.
Call your doctor for medical advice about side effects. You may report side effects to FDA at 1-800-FDA-1088.

How should I store CELEXA?

- Store CELEXA at room temperature between 68°F to 77°F (20°C to 25°C).
- Keep CELEXA and all medicines out of the reach of children.

General information about the safe and effective use of CELEXA
Medicines are sometimes prescribed for purposes other than those listed in a Medication Guide. Do not use CELEXA for a condition for which it was not prescribed. Do not give CELEXA to other people, even if they have the same symptoms that you have. It may harm them. You may ask your healthcare provider or pharmacist for information about CELEXA that is written for healthcare professionals.

What are the ingredients in CELEXA?
Active ingredient: citalopram hydrobromide
Inactive ingredients: copolyvidone, corn starch, crosscarmellose sodium, glycerin, lactose monohydrate, magnesium stearate, hypromellose, microcrystalline cellulose, polyethylene glycol, titanium dioxide and iron dioxide for coloring.
Distributed by:
AbbVie Inc.
1 N Waukegan Rd.
North Chicago, IL 60064
Licensed from H. Lundbeck A/S
© 2023 AbbVie. All rights reserved.
CELEXA and its design are trademarks of H Lundbeck A/S, used under license by AbbVie
For more information about CELEXA call 1-800-678-1605.

This Medication Guide has been approved by the U.S. Food and Drug Administration. Revised: 10/2023

20081725

PRINCIPAL DISPLAY PANEL

NDC 0456-4010-01
Celexa
citalopram
Tablets – 10 mg
Equivalent to 10 mg citalopram
100 Tablets

abbvie

PRINCIPAL DISPLAY PANEL

NDC 0456-4020-01
Celexa
citalopram
Tablets – 20 mg
Equivalent to 20 mg citalopram
100 Tablets

abbvie

PRINCIPAL DISPLAY PANEL

NDC 0456-4040-01
Celexa
citalopram
Tablets – 40 mg
Equivalent to 40 mg citalopram
100 Tablets

abbvie